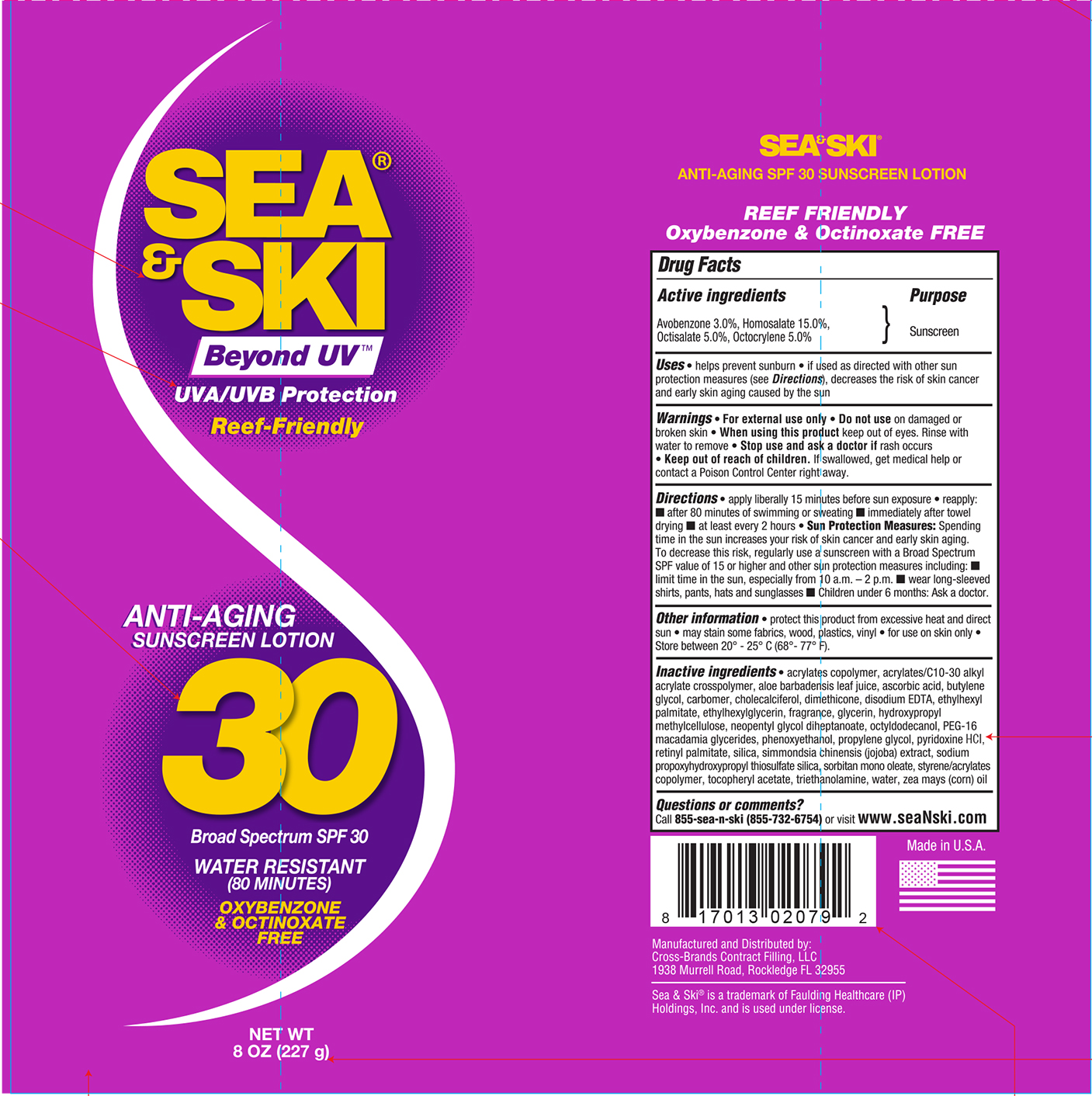 DRUG LABEL: Sea and Ski SPF 30
NDC: 73440-2079 | Form: LOTION
Manufacturer: Cross-Brands Contract FIlling
Category: otc | Type: HUMAN OTC DRUG LABEL
Date: 20210219

ACTIVE INGREDIENTS: HOMOSALATE 34.05 g/227 g; OCTOCRYLENE 11.35 g/227 g; AVOBENZONE 6.81 g/227 g; OCTISALATE 11.35 g/227 g
INACTIVE INGREDIENTS: WATER 118.27 g/227 g

Sea&Ski SPF 30 8oz